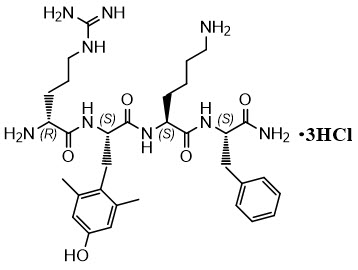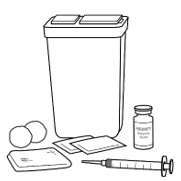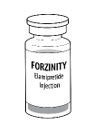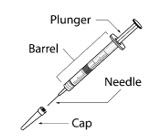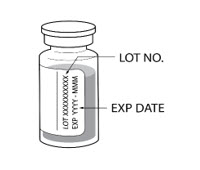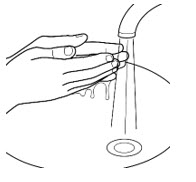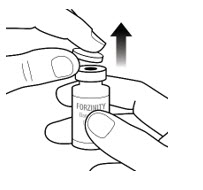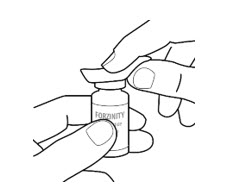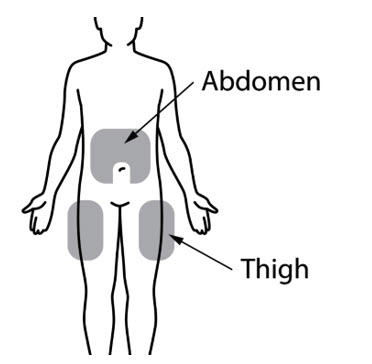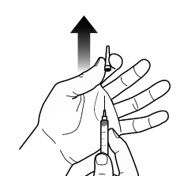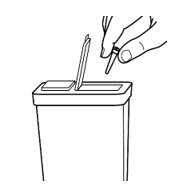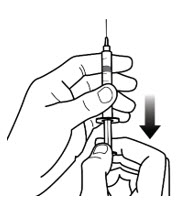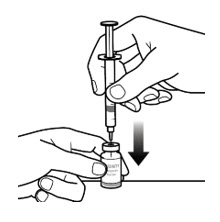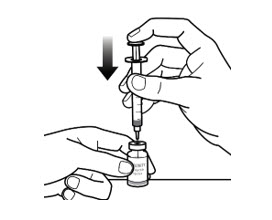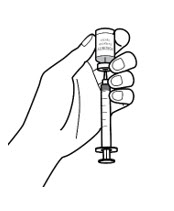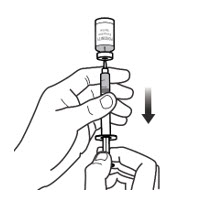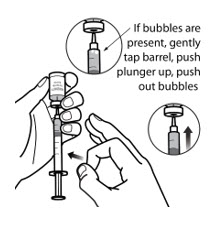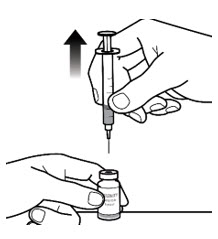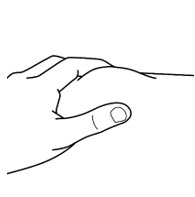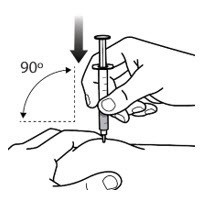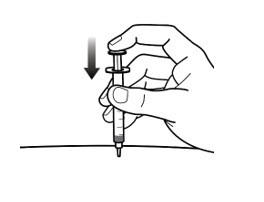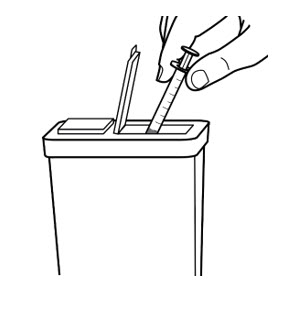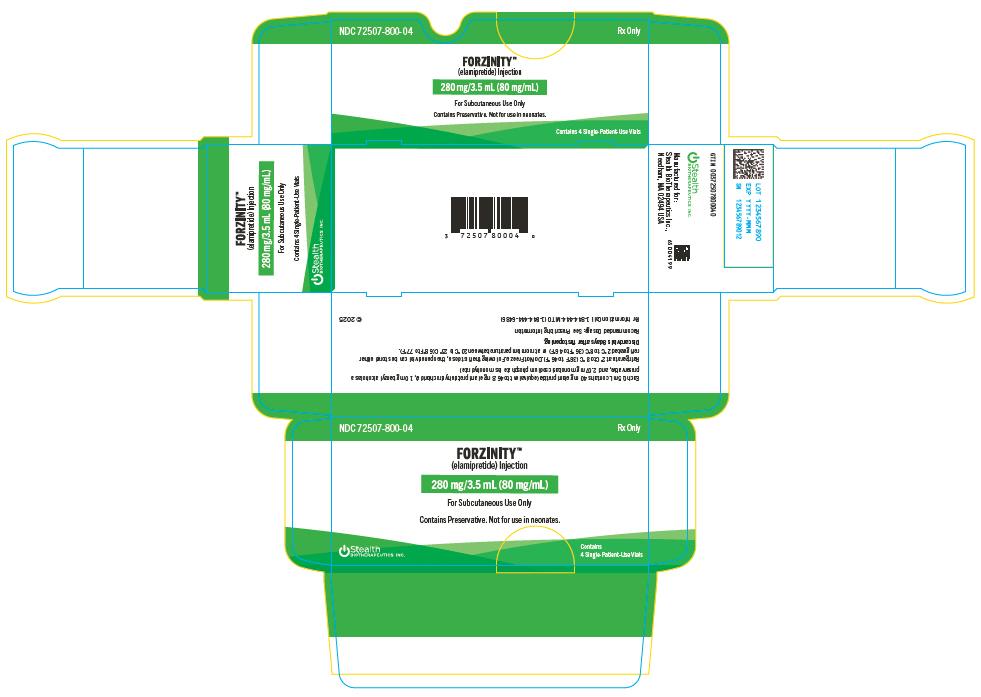 DRUG LABEL: FORZINITY
NDC: 72507-800 | Form: INJECTION
Manufacturer: Stealth Biotherapeutics Inc.
Category: prescription | Type: HUMAN PRESCRIPTION DRUG LABEL
Date: 20251210

ACTIVE INGREDIENTS: ELAMIPRETIDE HYDROCHLORIDE 280 mg/3.5 mL
INACTIVE INGREDIENTS: SODIUM PHOSPHATE, MONOBASIC, MONOHYDRATE; BENZYL ALCOHOL; HYDROCHLORIC ACID; SODIUM HYDROXIDE; WATER

HIGHLIGHTS OF PRESCRIBING INFORMATION

These highlights do not include all the information needed to use FORZINITY™ safely and effectively. See full prescribing information for FORZINITY.
FORZINITY (elamipretide) injection, for subcutaneous use
Initial U.S. Approval: 2025

1 INDICATIONS AND USAGE

FORZINITY™ is a mitochondrial cardiolipin binder indicated to improve muscle strength in adult and pediatric patients with Barth syndrome weighing at least 30 kg. (1)

This indication is approved under accelerated approval based on an improvement in knee extensor muscle strength, an intermediate clinical endpoint. (14) Continued approval for this indication may be contingent upon verification and description of clinical benefit in a confirmatory trial(s).

2 DOSAGE AND ADMINISTRATION

For patients weighing 30 kg and greater, the recommended dosage is 40 mg subcutaneously once daily. (2.1)

Reduce the dose in adults with severe renal impairment. (2.2, 8.6).

3 DOSAGE FORMS AND STRENGTHS

Injection: 280 mg/3.5 mL (80 mg/mL) solution for injection in single-patient-use vials. (3)

4 CONTRAINDICATIONS

Serious hypersensitivity to any of the ingredients (4, 5.2)

5 WARNINGS AND PRECAUTIONS

- Benzyl alcohol toxicity: Do not use in neonates. (5.1)

6 ADVERSE REACTIONS

Most common adverse reactions are injection site reactions. (6.1)

To report SUSPECTED ADVERSE REACTIONS, contact Stealth BioTherapeutics Inc. at 1-844-444-6486 or FDA at 1-800-FDA-1088 or www.fda.gov/medwatch.

FULL PRESCRIBING INFORMATION

1 INDICATIONS AND USAGE

FORZINITY is indicated to improve muscle strength in adult and pediatric patients with Barth syndrome weighing at least 30 kg.

This indication is approved under accelerated approval based on an improvement in knee extensor muscle strength, an intermediate clinical endpoint [see Clinical Studies (14)] . Continued approval for this indication may be contingent upon verification and description of clinical benefit in a confirmatory trial.

2 DOSAGE AND ADMINISTRATION

2.1 Recommended Dosage

The recommended dosage of FORZINITY in patients weighing at least 30 kg is 40 mg subcutaneously once daily.

Patients should receive the dose at the same time each day.

Missed Dose

If a dose is missed, skip the dose and take the next dose of FORZINITY at the scheduled time. Do not take a double dose of FORZINITY.

2.2 Dosage Modifications For Renal Impairment

Refer to Table 1 for dosage modifications in adults with renal impairment.

Table 1: Recommended Dosage in Adults with Renal Impairment
Estimated Glomerular Filtration Rate (eGFR) (mL/minute) | Recommended Dosage
Greater than or equal to 30 mL/minute | 40 mg subcutaneously once daily
Less than 30 mL/minute and NOT on dialysis | 20 mg subcutaneously once daily

There is insufficient information to recommend a dosage regimen in adults with eGFR less than 30 mL/minute and on dialysis.

There is insufficient information to recommend a dosage regimen in pediatric patients weighing 30 kg or greater with renal impairment.

2.3 Important Administration Instructions

FORZINITY is a clear, colorless to yellow aqueous solution that contains the preservative, benzyl alcohol. Visually inspect each vial of FORZINITY for particulate matter and cloudiness prior to administration, whenever solution and container permit. Do not use if the solution is cloudy or particulate matter is present.

Adult patients or caregivers may administer FORZINITY after proper training in preparing FORZINITY vials for administration, if a healthcare provider determines that it is appropriate, and with medical follow-up as necessary.

Use aseptic technique to prepare and administer FORZINITY. Administer FORZINITY by subcutaneous injection in the abdomen (at least 2 inches from the navel) or outer thigh and rotate the injection site daily. Do not inject where the skin is tender, bruised, red, or hard. Avoid injecting into scars or stretch marks. Refer to the Instructions for Use for preparation and administration.

FORZINITY is for single-patient-use only.

Do not mix other products in the same syringe.

Discard vials 8 days after first opening.

3 DOSAGE FORMS AND STRENGTHS

Injection: 280 mg/3.5 mL (80 mg/mL), sterile, clear, colorless to yellow aqueous solution for injection supplied as single-patient-use vials.

4 CONTRAINDICATIONS

Serious hypersensitivity to elamipretide or any of the excipients in FORZINITY [see Warnings and Precautions (5.2)].

5 WARNINGS AND PRECAUTIONS

5.1 Risk of Benzyl Alcohol Toxicity in Neonates

FORZINITY is not approved for use in neonates. Serious adverse reactions, including fatal reactions, of new onset or worsening metabolic acidosis that progressed to neurotoxicity, and in some cases gasping syndrome, have been reported in low-birth weight neonates (less than 2,500 grams) and preterm neonates (gestational age less than 34 weeks) who received benzyl alcohol (BA)-containing drugs intravenously. FORZINITY is not approved for intravenous use [see Dosage and Administration (2.1)] . Gasping syndrome is a life-threatening condition in neonates caused by BA toxicity and is primarily characterized by multiorgan dysfunction secondary to metabolic acidosis, which leads to gasping respirations and death. The minimum amount of BA at which these serious adverse reactions, including fatal reactions, may occur is not known (FORZINITY contains 20 mg of BA per mL). [See Use in Specific Populations (8.4).]

5.2 Hypersensitivity

Hypersensitivity reactions, including serious allergic reactions requiring emergency medical intervention, have been reported in patients receiving FORZINITY. These reactions have included skin manifestations such as rash, papular lesions, and eczematous dermatitis, as well as respiratory symptoms including cough [see Adverse Reactions (6.1)] . Reactions may occur within minutes to months after treatment initiation.

Monitor patients for signs and symptoms of hypersensitivity reactions during treatment. If a serious hypersensitivity reaction occurs, do not administer further doses of FORZINITY and institute appropriate emergency treatment, including epinephrine, antihistamines, and corticosteroids as clinically indicated. Patients who have experienced a serious hypersensitivity reaction should not be rechallenged with FORZINITY [see Contraindications (4)] .

For mild to moderate skin reactions, consider treatment with topical corticosteroids and oral antihistamines. Consider discontinuation of FORZINITY if persistent or severe skin reactions develop.

6 ADVERSE REACTIONS

6.1 Clinical Trials Experience

Because clinical trials are conducted under widely varying conditions, adverse reaction rates observed in the clinical trials of a drug cannot be directly compared to rates in the clinical trials of another drug and may not reflect the rates observed in practice.

In the FORZINITY clinical development program, 12 male patients aged 12 to 35 years with genetically-confirmed Barth syndrome received treatment with daily subcutaneous injections of 40 mg FORZINITY. Eleven of these 12 patients were Caucasian.

Patients first participated in a double-blind, placebo-controlled crossover trial where they were randomized to one of two sequences:

- 12 weeks of FORZINITY in Period 1 then a 4-week washout followed by 12 weeks of placebo in Period 2 or
- 12 weeks of placebo in Period 1 then a 4-week washout followed by 12 weeks of FORZINITY in Period 2

Ten patients completed the randomized trial and entered the open-label extension period where they received FORZINITY once daily. Eight of these patients received FORZINITY for 168 weeks, three of whom received FORZINITY for a total of 192 weeks.

Adverse reactions occurring more commonly on FORZINITY than on placebo include injection site reactions such as injection site erythema, pain, induration, pruritus, bruising, and urticaria (Table 2).

Table 2: Summary of Adverse Drug Reactions in the Placebo-Controlled Crossover Study, Barth Safety Population
 | Combined
 | (Periods 1 and 2)
 | Elamipretide | Placebo
 | N=12 | N=12
 | n (%) | n (%)
Any local administration reaction | 12 (100) | 8 (67)
Injection site erythema | 12 (100) | 3 (25)
Injection site induration | 8 (67) | 2 (17)
Injection site pruritus | 8 (67) | 2 (17)
Injection site pain | 9 (75) | 5 (42)
Injection site bruising | 3 (25) | 0
Injection site urticaria | 3 (25) | 0
Injection site hemorrhage | 0 | 1 (8)

Eosinophilia

Increases in absolute eosinophil counts were noted frequently in studies where duration of administration of FORZINITY was 30 days or greater. Eosinophil counts generally peaked around 90 days after initial exposure (mean increase from baseline ~0.5 to 0.6 × 10^3/uL) and returned to baseline levels after 6 to 12 months of continuous exposure or after discontinuation of FORZINITY. The elevation in eosinophils was not associated with clinical manifestations or changes in other laboratory parameters.

8 USE IN SPECIFIC POPULATIONS

8.1 Pregnancy

Risk Summary

Barth Syndrome is a rare, X-linked, recessive, genetic disorder and is not likely to affect females. Therefore, there are no data with FORZINITY use in pregnant women to evaluate for a drug-related risk of major birth defects, miscarriage, or other adverse maternal or fetal outcomes. In animal reproduction studies, no adverse developmental outcomes occurred at any dose tested (see Data). FORZINITY contains benzyl alcohol as a preservative. Because benzyl alcohol is rapidly metabolized by a pregnant woman, benzyl alcohol exposure in the fetus is unlikely.

The background risk of major birth defects and miscarriage for the indicated population is unknown. All pregnancies have a background risk of birth defect, loss, or other adverse outcomes. In the U.S. general population, the estimated background risk of major birth defects and miscarriage in clinically recognized pregnancies is 2 to 4% and 15 to 20%, respectively.

Data

Animal Data

In pregnant rats, once-daily intravenous infusion of elamipretide during the period of organogenesis [gestation day (GD) 7 to GD 17] did not result in embryo-fetal developmental toxicity at doses tested up to 10 mg/kg/day, approximately 4 times the clinical exposure at the maximum recommended human dose (MRHD) of 40 mg/day, based on area under the concentration-time curve (AUC).

In pregnant rabbits, intravenous infusion with elamipretide once daily during the period of organogenesis (GD 7 to GD 19) did not result in embryo-fetal developmental toxicity at doses tested up to 50 mg/kg/day, approximately 10 times the clinical exposure at the MRHD, based on AUC.

In a pre- and postnatal study in rats, elamipretide was subcutaneously administered at doses of 0, 5, 10 or 15 mg/kg/day throughout pregnancy and lactation (GD 6 to Lactation Day 20). No adverse developmental effects were observed at doses up to 15 mg/kg/day, approximately 6-times the clinical exposure at the MRHD, based on AUC.

8.2 Lactation

Risk Summary

Barth Syndrome is a rare, X-linked, recessive, genetic disorder and is not likely to affect females. Therefore, there is no data to evaluate the presence of FORZINITY in human milk, the effect on the breastfed infant, or the effects on milk production.

FORZINITY contains benzyl alcohol. Because benzyl alcohol is rapidly metabolized by a lactating female, benzyl alcohol exposure in the breastfed infant is unlikely. The developmental and health benefits of breastfeeding should be considered along with the mother's clinical need for FORZINITY and any potential adverse effects on the breastfed infant from FORZINITY or from the underlying maternal condition.

8.4 Pediatric Use

The safety and effectiveness of FORZINITY to improve muscle strength have been established in pediatric patients with Barth syndrome weighing at least 30 kg. Use of FORZINITY for this indication is supported by improvement in knee extensor muscle strength, an intermediate clinical endpoint, observed in an open-label extension study of FORZINITY that included seven pediatric patients aged 12 years and older. [see Dosage and Administration (2.1), and Clinical Studies (14)] .

The safety and effectiveness of FORZINITY have not been established in pediatric patients weighing less than 30 kg.

FORZINITY is not approved for use in neonates. Serious adverse reactions, including fatal reactions, of new onset or worsening metabolic acidosis that progressed to neurotoxicity, and in some cases gasping syndrome, have been reported in low-birth weight neonates and preterm neonates who received BA containing drugs intravenously (FORZINITY is not approved for intravenous use) [see Dosage and Administration (2.1)] . Gasping syndrome is a life-threatening condition in neonates caused by BA toxicity that is characterized by new onset or worsening metabolic acidosis with gradual neurological deterioration, seizures, intracranial hemorrhage, hematologic abnormalities, skin breakdown, hepatic and renal failure, hypotension, bradycardia, and gasping respirations followed by death. In reported cases, BA in amounts of 99 to 234 mg/kg/day produced blood BA levels of 6.6 to 14.9 mg/dL, but the minimum amount of BA at which gasping syndrome may occur in neonates is not known (FORZINITY contains 20 mg of BA per mL) [see Warnings and Precautions (5.1)] .

8.5 Geriatric Use

Clinical studies of FORZINITY did not enroll subjects with Barth syndrome aged 65 years and older.

8.6 Renal Impairment

No dosage adjustment is required for patients with mild (eGFR 60 to 89 mL/min) or moderate (eGFR 30 to 59 mL/min) renal impairment. The FORZINITY dose should be reduced by one half administered subcutaneously once daily in adults with severe renal impairment (eGFR less than 30 mL/min) who are not on dialysis [see Dosage and Administration (2.2)] . FORZINITY has not been studied in patients with renal failure on dialysis [see Clinical Pharmacology (12.3)] .

10 OVERDOSAGE

There were no reports of overdose during clinical trials with FORZINITY. Symptoms and signs of overdose are likely to be histamine-related (e.g., decreased blood pressure, presyncope) and should be managed according to standard of care. Interrupt treatment with FORZINITY if there is suspicion of overdose.

11 DESCRIPTION

FORZINITY contains elamipretide, a mitochondrial cardiolipin binder. Elamipretide is isolated as a hydrochloride salt that is freely soluble in water. The chemical name for elamipretide hydrochloride is L-Phenylalaninamide, D-arginyl-2,6-dimethyl-L-tyrosyl-L-lysyl-, hydrochloride (1:3). Its molecular formula is C32H49N9O5∙3HCl and its molecular weight is 749.2.

The structure of elamipretide hydrochloride is:

All amino acid residues in FORZINITY have the L configuration except for arginine which has the D configuration. The peptide sequence is denoted as D-Arg-2,6-dimethyl-Tyr-Lys-Phe-NH2.

FORZINITY is a ready-to-use sterile, clear, colorless to yellow aqueous solution supplied as single-patient-use vials containing 3.5 mL solution for subcutaneous injection. Each 0.5 mL dose of FORZINITY contains 40 mg of elamipretide (equivalent to 46.8 mg elamipretide hydrochloride), 10 mg benzyl alcohol as a preservative, and 2.07 mg monobasic sodium phosphate (as monohydrate). The product may contain hydrochloric acid or sodium hydroxide to adjust pH. The pH of FORZINITY solution is 4.7 to 6.1.

12 CLINICAL PHARMACOLOGY

12.1 Mechanism of Action

FORZINITY is a mitochondrial cardiolipin binder that localizes to the inner mitochondrial membrane and improves mitochondrial morphology and function.

12.2 Pharmacodynamics

Effects on QTc Interval

Cardiac electrophysiology

Clinically significant QTc interval prolongation was not observed at 3 times the peak concentration of the maximum recommended FORZINITY dose.

12.3 Pharmacokinetics

Elamipretide exposure increases proportionally over a dose range of 2 to 80 mg following daily subcutaneous injections with minimal accumulation.

Absorption

Maximum elamipretide concentrations were reached between 0.5 to 1 hour after subcutaneous administration. The absolute bioavailability following subcutaneous administration is approximately 92%. FORZINITY exposure is comparable after subcutaneous injection to the thigh or to the abdomen.

Distribution

Elamipretide is distributed throughout total body water with an approximate volume of distribution of 0.5 L/kg. There is low binding to plasma proteins (approximately 39%).

Elimination

Metabolism

Elamipretide is metabolized via sequential C-terminal degradation to the M1 tripeptide and M2 dipeptide metabolites, which do not have pharmacological activity.

Excretion

Elamipretide and its metabolites M1 and M2 are excreted in the urine. At 48 hours post-dose, approximately 100% of the FORZINITY dose was recovered in the urine as either elamipretide, M1, or M2 in patients with normal renal function.

Specific Populations

Patients with Renal Impairment

Elamipretide exposure (AUC) increased by 39% in subjects with creatinine clearance 60 to 89 mL/min, 75% in subjects with creatinine clearance 30 to 59 mL/min, and 125% in subjects with creatinine clearance less than 30 mL/min not on dialysis. Renal impairment was categorized based on 24-hour measured urinary creatinine clearance. There was minimal accumulation of elamipretide with daily dosing, regardless of the severity of renal impairment. There was a significant increase in exposure of the M1 and M2 metabolites, up to 280% and 640%, respectively, in subjects with severe renal impairment not on dialysis (creatinine clearance less than 30 mL/min).

While the effect of renal impairment on elamipretide pharmacokinetics was characterized using 24-hour measured urinary creatinine clearance, analyses conducted with estimated glomerular filtration (CKD-EPI equation) support the recommendations for use in this specific population [see Dosage and Administration (2.2)and Use in Specific Populations (8.6)] .

Patients with Hepatic Impairment

No hepatic metabolism was observed for elamipretide in vitro.Hepatic impairment is not expected to alter the pharmacokinetics (PK) of elamipretide.

Drug Interaction Studies

In Vitro Studies

CYP enzymes: Elamipretide does not inhibit CYP1A, CYP2D6, CYP2E1, CYP2B6, CYP2C8, CYP2C9, CYP2C19, or CYP3A. Elamipretide does not induce metabolism by CYP1A2, CYP2B6, or CYP3A4.

Drug transporters: Elamipretide does not inhibit the activity of OCT2, BCRP, OAT1, OAT3, OATP1B1, OATP1B3, P-gp, or MATE2-K. Elamipretide is an inhibitor of MATE1 (IC503.53 μM).

In Vivo Clinical Studies

Aspirin: administration of elamipretide (0.1 mg/kg/hour for 4 hours via intravenous infusion) starting 4 hours after a single dose of 650 mg aspirin did not affect the PK of aspirin and its metabolite, salicylic acid. There was no impact on the antiplatelet activity of aspirin when co-administered with elamipretide.

Clopidogrel: administration of elamipretide (0.1 mg/kg/hour for 4 hours via intravenous infusion) starting 4 hours after a single dose of 300 mg clopidogrel did not significantly affect the PK of clopidogrel. There was no impact on the anti-thrombotic activity of clopidogrel when co-administered with elamipretide.

Unfractionated heparin: administration of elamipretide (0.25 mg/kg/hour for 4 hours via intravenous infusion) had no significant impact on activated partial thromboplastin time (aPTT) and anti-factor Xa activity of unfractionated heparin, when co-administered 7 hours after starting the unfractionated heparin infusion.

13 NONCLINICAL TOXICOLOGY

13.1 Carcinogenesis, Mutagenesis, Impairment of Fertility

Carcinogenicity studies have not been conducted with elamipretide.

Elamipretide was negative in an in vitrobacterial reverse mutation assay, a chromosomal aberration assay in Chinese hamster ovary cells, and an in vivorat bone marrow micronucleus assay.

Subcutaneous doses of elamipretide in rats of up to 20 mg/kg/day, approximately 5-times the clinical exposure at the MRHD of 40 mg, did not adversely affect fertility or reproductive performance.

14 CLINICAL STUDIES

FORZINITY was evaluated in a randomized, double-blind, placebo-controlled, crossover trial and its 192-week, open-label, single-arm extension period.

The randomized trial evaluated the efficacy and safety of once daily FORZINITY 40 mg injected subcutaneously for 12 weeks in 12 subjects ≥12-years-old and >30 kg with genetically confirmed Barth syndrome. The primary endpoints for the randomized trial were distance walked during 6-minute walk test and Total Fatigue Score on the Barth syndrome Symptom Assessment. FORZINITY was not superior to placebo on these primary endpoints. Ten subjects completed the randomized trial and entered the extension period designed to evaluate long-term safety and tolerability of FORZINITY. Eight of these 10 subjects participated through Week 168 of the extension period.

Knee extensor muscle strength measured by handheld dynamometry was evaluated as one of the secondary endpoints in the randomized trial and in the extension period. Increases in knee extensor muscle strength were not observed during the randomized trial but were observed during the extension period. At the pre-dose baseline visit at the start of the randomized trial, median (min, max) muscle strength was 124 (92, 176) newtons. Table 3 shows descriptive changes from pre-dose baseline for knee extensor muscle strength during the randomized controlled trial and extension period.

Table 3. Descriptive Statistics, Changes from Baseline [All descriptive statistics use the muscle strength measurement obtained immediately prior to the first dose of study medication at the beginning of Period 1 of the randomized controlled trial as baseline] in Muscle Strength (newtons)
 | Visit | N | Median Change | Min, Max Change
Randomized Controlled Trial | Week 12 Placebo | 12 | -5 | -31, 48
Randomized Controlled Trial | Week 12 Elamipretide | 12 | 4 | -41, 86
Open-Label Extension Period | Week 12 | 10 | 34 | 7, 95
Open-Label Extension Period | Week 24 | 9 | 68 | 3, 90
Open-Label Extension Period | Week 36 | 8 | 57 | 9, 92
Open-Label Extension Period | Week 48 | 8 | 41 | -2, 144
Open-Label Extension Period | Week 72 | 8 | 35 | -4, 100
Open-Label Extension Period | Week 168 | 8 | 63 | 38, 78

16 HOW SUPPLIED/STORAGE AND HANDLING

16.1 How Supplied

FORZINITY (elamipretide) injection is a sterile, clear, colorless to yellow aqueous solution supplied as:

- Carton containing four 280 mg/3.5 mL (80 mg/mL) single-patient-use vials (NDC 72507-800-04)

16.2 Storage

Store refrigerated at 2°C to 8°C (36°F to 46°F). Do not freeze. Following the first dose, the opened vial can be stored either refrigerated 2°C to 8°C (36°F to 46°F) or at room temperature between 20°C to 25°C (68°F to 77°F). Discard vials 8 days after first opening.

17 PATIENT COUNSELING INFORMATION

Advise the patient and caregiver to read the FDA-approved patient labeling (Instructions for Use).

Instruct patients and caregivers to discard vials 8 days after first opening.

Instruct patients and caregivers on how to prepare and administer the correct dose of FORZINITY using aseptic technique. Instruct patients and caregivers to administer FORZINITY by subcutaneous injection in the abdomen (at least 2 inches from the navel) or outer thigh and to rotate the injection site daily according to the Instructions for Use. Instruct patients and caregivers not to inject where the skin is tender, bruised, red, or hard and to avoid injecting into scars or stretch marks.

Inform patients and caregivers that injection site reactions such as erythema, pain, induration, pruritus, bruising, or urticaria can be treated with antihistamines or topical corticosteroids.

Advise the patient and caregiver to discontinue FORZINITY and seek immediate medical attention if any signs or symptoms of an immediate hypersensitivity reaction occur [see Warnings and Precautions (5.2)] .

FORZINITY manufactured for:
Stealth BioTherapeutics Inc.
Needham, MA 02494

FORZINITY™ (elamipretide) is a trademark of Stealth BioTherapeutics Inc.

This product is covered by one or more of the following US Patents: US 7,576,061, US 7,550,439, US 9,687,519, US 11,083,771, US 11,083,772, US 11,771,734

PATIENT INFORMATION

INSTRUCTIONS FOR USE
FORZINITY™ [for zin' i tee]
(elamipretide)
injection

This Instructions for Use contains information on how to inject FORZINITY. Read this Instructions for Use before you inject a dose of FORZINITY for the first time and each time you get a refill. This information does not take the place of talking to your healthcare provider about your medical condition or treatment. Ask your healthcare provider about any instructions you do not understand.

Important information you need to know before preparing and injecting FORZINITY:

- Your or your child's healthcare provider will show you how to prepare and inject FORZINITY before you use the vial for the first time. It is recommended that FORZINITY injections be prepared and given by adults or adult caregivers.
- FORZINITY is for injection under the skin (subcutaneous injection).
- FORZINITY is injected 1 time each day, at the same time each day.
- If a dose of FORZINITY is missed, skip that dose, and take the next dose of FORZINITY at the next scheduled time. Do not double a dose of FORZINITY.
- FORZINITY vial contains enough medicine for more than 1 dose.
- Do notmix FORZINITY with other medicines in the same syringe.
- Only use disposable syringes and needles prescribed by your healthcare provider or included with your medicine. Using the wrong syringe can lead to a mistake in your dose and you could inject too much or too little FORZINITY.
- Always use a new disposable syringe and needle for each injection.
- Do notreuse or share your needles with other people.
- Check the package containing the disposable syringe. If the package has been opened or damaged, do not use the syringe. Throw away the damaged syringe in an FDA-cleared sharps disposal container. See Step 8: "Throw away (dispose of) used needles and syringes."

Storing FORZINITY

- Store unused vials of FORZINITY in the refrigerator between 36°F to 46°F (2°C to 8°C).
- After the first dose, store opened vials in the refrigerator between 36°F to 46°F (2°C to 8°C) or at room temperature between 68°F to 77°F (20°C to 25°C).
- Do notfreeze FORZINITY vials.
- Throw away FORZINITY vials 8 days after first opening, even if some medicine is still left in the vial.

Keep FORZINITY, needles, disposable syringes, and all medicines out of the reach of children.

When using a new vial of FORZINITY:

- Remove the carton from the refrigerator.
- Make sure the name FORZINITY appears on the carton labeling.
- Make sure the tamper evident seal is on the carton.
- Remove the vial from the carton.
- Allow the vial to sit at room temperature for at least 10 minutes.
- Remove the "Instructions for Use" from the carton.
- Write the "Discard After" date on the vial. Repeat this step for each new vial you open.
- Return the carton containing unused vials to the refrigerator.

Step 1: Gather the following supplies on a clean flat, work surface (See Figure 1-A)

- 1 vial of FORZINITY (See Figure 1-B). If using an opened vial stored in a refrigerator, allow the opened vial to sit at room temperature for at least 10 minutes.

The following supplies are not included in the carton:

- 1 new disposable syringe with the needle attached for each injection (See Figure 1-C)
- 2 alcohol wipes
- cotton ball or gauze pad
- sharps disposal container

Figure 1-A

Figure 1-B

Figure 1-C

Step 2: Check your FORZINITY vial

- Make sure the name FORZINITY (elamipretide) appears on the vial label.
- Check the expiration date (EXP) on the vial label (See Figure 2). Do notuse after the expiration date (EXP) on label.
- Do notuse beyond the "Discard After" date written on the vial.
- Make sure that the liquid in the vial is clear, colorless to yellow. Do notuse if the liquid is discolored or cloudy, or if the liquid has lumps, flakes, or particles.
- Do notuse if the glass vial has cracks.
- Do notuse if the plastic cap on a new vial is broken or missing.

Figure 2

Step 3: Prepare the vial

- Wash your hands well with soap and water (See Figure 3-A)
- Remove the plastic cap on the vial (if using a new vial) (See Figure 3-B). Throw away the plastic cap in the household trash.
- Clean the top of the vial stopper with an alcohol wipe before each injection (See Figure 3-C).
- Throw away the alcohol wipe in the household trash.

Figure 3-A

Figure 3-B

Figure 3-C

Step 4: Prepare the injection site

FORZINITY is injected directly into a layer of fat under your skin (subcutaneous injection).

- Choose 1 of the following injection sites (See Figure 4).
  - stomach-area (abdomen), 2 inches away from belly button
  - outer area of the thigh
- Change (rotate) the injection site daily with each injection to reduce the risk of skin problems. You may want to use a calendar or diary to record your injection sites.
- Do notinject or give injections in the same location sites as other medicines.
- Do notinject or give FORZINITY injections into areas where the skin is tender, red, bruised, hard, scarred or has stretch marks.

Figure 4

Clean the injection site with the second alcohol wipe.

- Do nottouch, fan, or blow on the cleaned area.
- Wait for about 10 seconds for the area to dry.

Step 5: Prepare syringe

- Hold the syringe by the barrel with the needle cap pointing up and carefully pull the needle cap straight off and away from your body (See Figure 5-A).
- Throw the needle cap into the sharps disposal container (See Figure 5-B).
- Fill the syringe with air by pulling back on the plunger to the prescribed dose in milliliters (mL) (See Figure 5-C).
- With the vial on a flat work surface and in the upright position, insert the needle straight down into the center of the vial rubber stopper (See Figure 5-D).
- Slowly inject all the air from the syringe into the vial (See Figure 5-E).

Figure 5-A

Figure 5-B

Figure 5-C

Figure 5-D

Figure 5-E

Step 6: Withdraw the dose

- Keep the needle inside the vial. Turn the vial and syringe upside down with 1 hand. Keep needle tip in the liquid (See Figure 6-A).
- Slowly pull back on the plunger to withdraw your prescribed dose into the syringe (See Figure 6-B). Be careful not to pull the plunger out of the syringe.
- Keep the needle inside the vial. Check for air bubble(s). Small air bubble(s) are normal. Large amounts of air bubble(s) may give you the wrong dose of FORZINITY.
- If there are large air bubble(s), then gently tap the side of the syringe with your fingers until the large air bubble(s) rises to the top of the syringe (See Figure 6-C).
- Slowlypush the plunger up to push the large air bubble(s) back into the vial (See Figure 6-C).
- If no large air bubbles are present, gently pull back on the plunger again more slowly to fill the syringe to your prescribed dose.
- Return the vial to an upright position and place it on the clean, flat work surface.
- While holding the vial with 1 hand and the barrel of the syringe between the fingertips of your other hand, pull the needle straight out of the vial (See Figure 6-D).
- Keep the syringe in your hand. Do notset it down.

Figure 6-A

Figure 6-B

Figure 6-C

Figure 6-D

Step 7: Take or give the injection

- With 1 hand, pinch about 2 inches of skin at the injection site between your thumb and index (pointer) finger (See Figure 7-A). Pinching the skin helps to make sure that you inject the medicine under the skin (subcutaneous).
- With the other hand, hold the middle of the syringe at a 90º degree angle to your body and insert the needle into the folded skin between the thumb and index (pointer) finger (See Figure 7-B).
- Maintaining the 90º degree angle to your body, push the needle straight into the injection site (See Figure 7-B).
- Make sure that you push the needle all the way into the skin. Do nothold or push on the plunger while inserting the needle.
- After the needle is inserted, the skin no longer needs to be pinched.
- Inject the solution by gently pushing the syringe plunger all the way until the syringe is empty (See Figure 7-C).
- Take the needle out of your skin at the same angle you inserted it. Keep the plunger pushed in while removing the needle.
- If there is bleeding, lightly press a cotton ball or gauze pad over the injection site.

Figure 7-A

Figure 7-B

Figure 7-C

Step 8: Throw away (dispose of) used needles and syringe

- Throw away used alcohol wipes in the household trash.
- Do not put the needle cover back on the needle or replace the needle.
- Do not throw away (dispose of) needles and syringes in your household trash.
- Throw away used needles and syringes in an FDA-cleared sharps disposal container right away after use (See Figure 8).
- If you do not have an FDA-cleared sharps disposal container, you may use a household container that is:
  - made of heavy-duty plastic,
  - can be closed with a tight-fitting, puncture-resistant lid, without sharps being able to come out,
  - upright and stable during use,
  - leak-resistant, and
  - properly labeled to warn of hazardous waste inside the container.
- When your sharps disposal container is almost full, you will need to follow your community guidelines for the right way to dispose of your sharps disposal container. There may be state or local laws about how you should throw away used needles and syringes. For more information about safe sharps disposal, and for specific information about sharps disposal in the state that you live in, go to the FDA's website at:
  http://www.fda.gov/safesharpsdisposal Do not dispose of your used sharps disposal container in your household trash unless your community guidelines permit this. Do not recycle your used sharps disposal container.

Figure 8

FORZINITY manufactured for:
Stealth BioTherapeutics Inc.
Needham, MA 02494

This Instructions for Use has been approved by the U.S. Food and Drug Administration. Issued: 9/2025

PRINCIPAL DISPLAY PANEL - 3.5 mL Vial Carton

NDC 72507-800-04
Rx Only

FORZINITY™
(elamipretide) Injection

280 mg/3.5 mL (80 mg/mL)

For Subcutaneous Use Only

Contains Preservative. Not for use in neonates.

Contains 4 Single-Patient-Use Vials